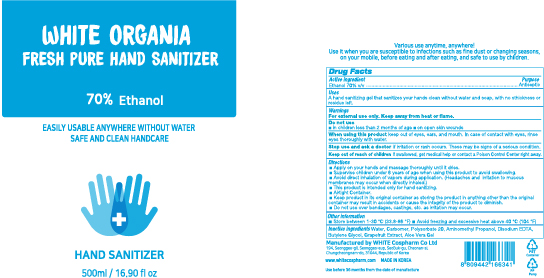 DRUG LABEL: WHITE ORGANIA FRESH PURE HAND SANITIZER
NDC: 75312-0500 | Form: GEL
Manufacturer: WHITE COSPHARM CO.,LTD.
Category: otc | Type: HUMAN OTC DRUG LABEL
Date: 20200417

ACTIVE INGREDIENTS: ALCOHOL 350 mL/500 mL
INACTIVE INGREDIENTS: AMINOMETHYLPROPANOL; POLYSORBATE 20; GRAPEFRUIT; EDETATE DISODIUM; CARBOMER HOMOPOLYMER, UNSPECIFIED TYPE; WATER; BUTYLENE GLYCOL; ALOE VERA LEAF

WHITE ORGANIA FRESH PURE HAND SANITIZER 500 ml